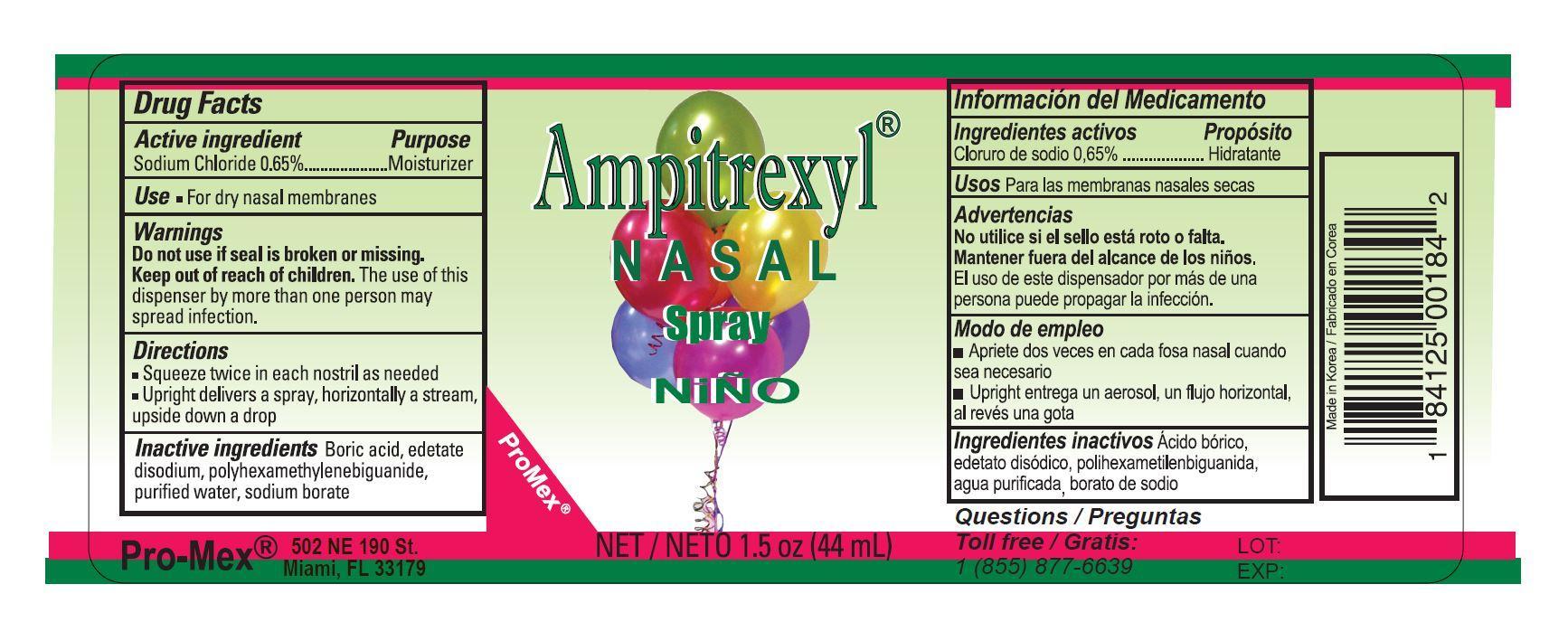 DRUG LABEL: Saline Nasal 
NDC: 58988-0184 | Form: SPRAY
Manufacturer: Promex, LLC
Category: otc | Type: HUMAN OTC DRUG LABEL
Date: 20131209

ACTIVE INGREDIENTS: SODIUM CHLORIDE 6.5 mg/1 mL
INACTIVE INGREDIENTS: BORIC ACID; EDETATE DISODIUM; POLYAMINOPROPYL BIGUANIDE; WATER; SODIUM BORATE

Drug Facts

ACTIVE INGREDIENT

Sodium Chloride 0.65%

Purpose

Moisturizer

Use

- For dry nasal membranes

Warnings

Do not use if seal is broken or missing.

Keep out of reach of children

The use of this dispenser by more than one person may spread infection.

Directions

- Squeeze twice in each nostril as needed
- Upright delivers a spray, horizontally a stream, upside down a drop

Inactive Ingredients

Boric acid, edetate disodium, polyhexamethylenebiguanide, purified water, sodium borate

PACKAGE LABEL

saline nasal spray